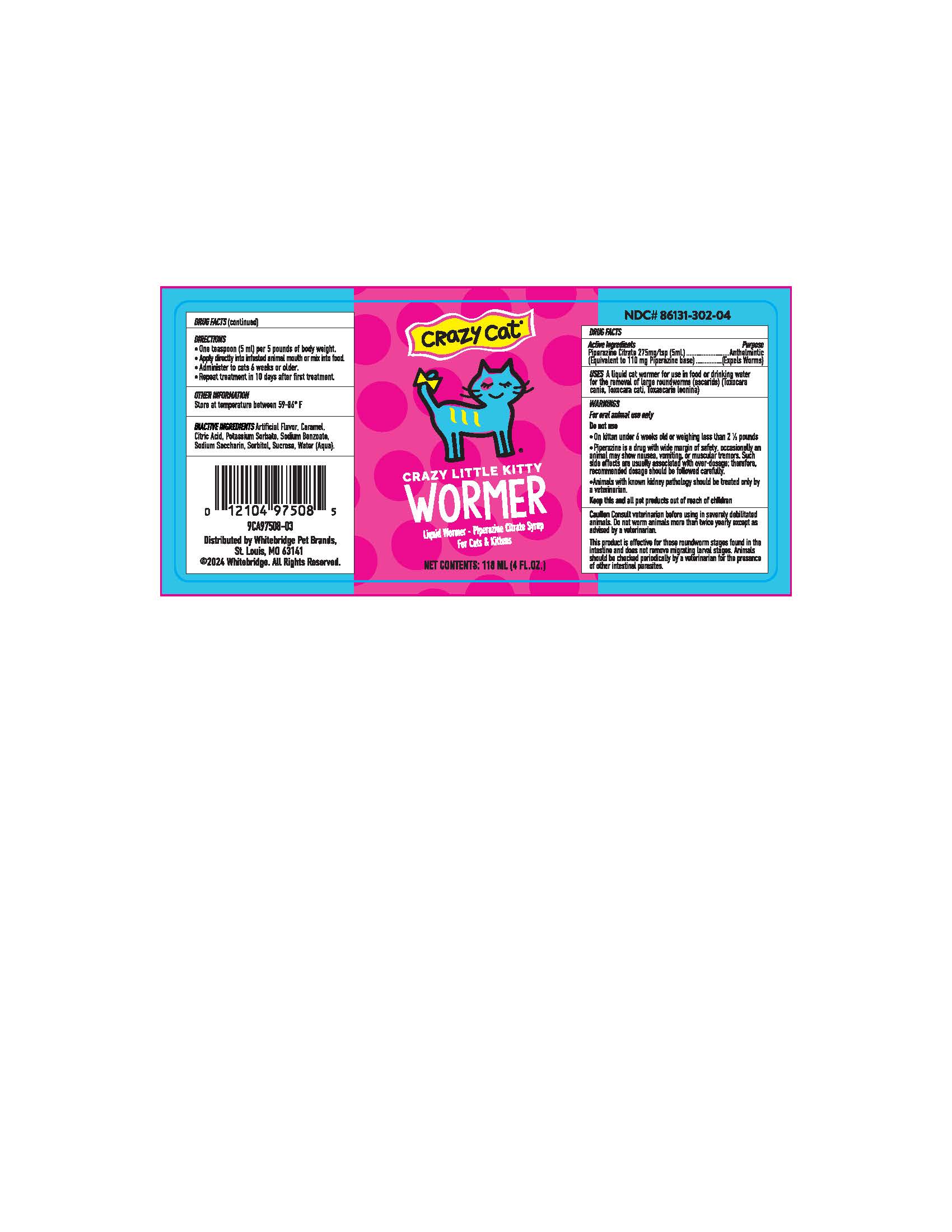 DRUG LABEL: Wormicide
NDC: 86131-302 | Form: SYRUP
Manufacturer: Whitebridge Pet Brands
Category: animal | Type: OTC ANIMAL DRUG LABEL
Date: 20260123

ACTIVE INGREDIENTS: PIPERAZINE CITRATE 5.5 g/100 mL
INACTIVE INGREDIENTS: WATER; SUCROSE; SORBITOL; SACCHARIN SODIUM; CARAMEL; CITRIC ACID MONOHYDRATE; POTASSIUM SORBATE; SODIUM BENZOATE

Crazy Little Kitty Wormer

DRUG FACTS

Active Ingredients

Piperazine Citrate 275 mg/tsp (5ml)

(Equivalent to 100 mg Piperazine Base

Purpose

Anthelmintic (Expels Worms)

Uses

A liquid cat wormer for use in food or drinking water for the removal of large roundworms (ascards) (Toxocara canis, Tococara cati, Toxocaris leonina)

Warnings

For oral animal use only.

Do not use

- On kitten under 6 weeks old or weighing less than 2 1/2 pounds
- Piperazine is a drug with a wide margin of saftey, occasionally an animal may show nausea, vomiting, or muscular tremors. Such side effects are usually associated with over-dosage; therefore, recommended dosage should be followed carefully.
- Animals with know kidnet pathology should be treated only by a veterianarian.

Keep this and all other per products out of reach of children.

Cautions

Consult a veterinarian before using in severly debilitated animals. Do not worm animals more than twice yearly except as advised by a veterinarian. This product is effective for those roundworms stages found in the intestine and does not remove migrating larval stages. Animals should be checked periodically by a veterinarian for the presence of other intestinal parasites.

Directions

- One teaspoon (5 ml) per 5 pounds of body weight
- Apply directly into infested animals mouth or mix into food.
- Administer to cats 6 weeks or older
- Repeat treatment in 10 days after first treatment

Other Information

Store at temperatures between 59 - 86 F

Inactive Ingredients

Artifical Flavor, Caramel, Citric Acid, Potassium Sorbate, Sodium Benzoate, Sodium Saccharin, Sorbitiol, Sucrose, Water (Aqua).

Distrubuted by Whitebridge Pet Brands

St. Louis, MO 63141

2023 Whitebridge. All Right Reserved.

PACKAGE LABEL

Crazy Cat

Crazy Little Kitty Wormer

Liquid Wormer - Piperazine Citrate Syrup

For Cats & Kittens

Net Contents: 118 ml (4 Fl. OZ.)